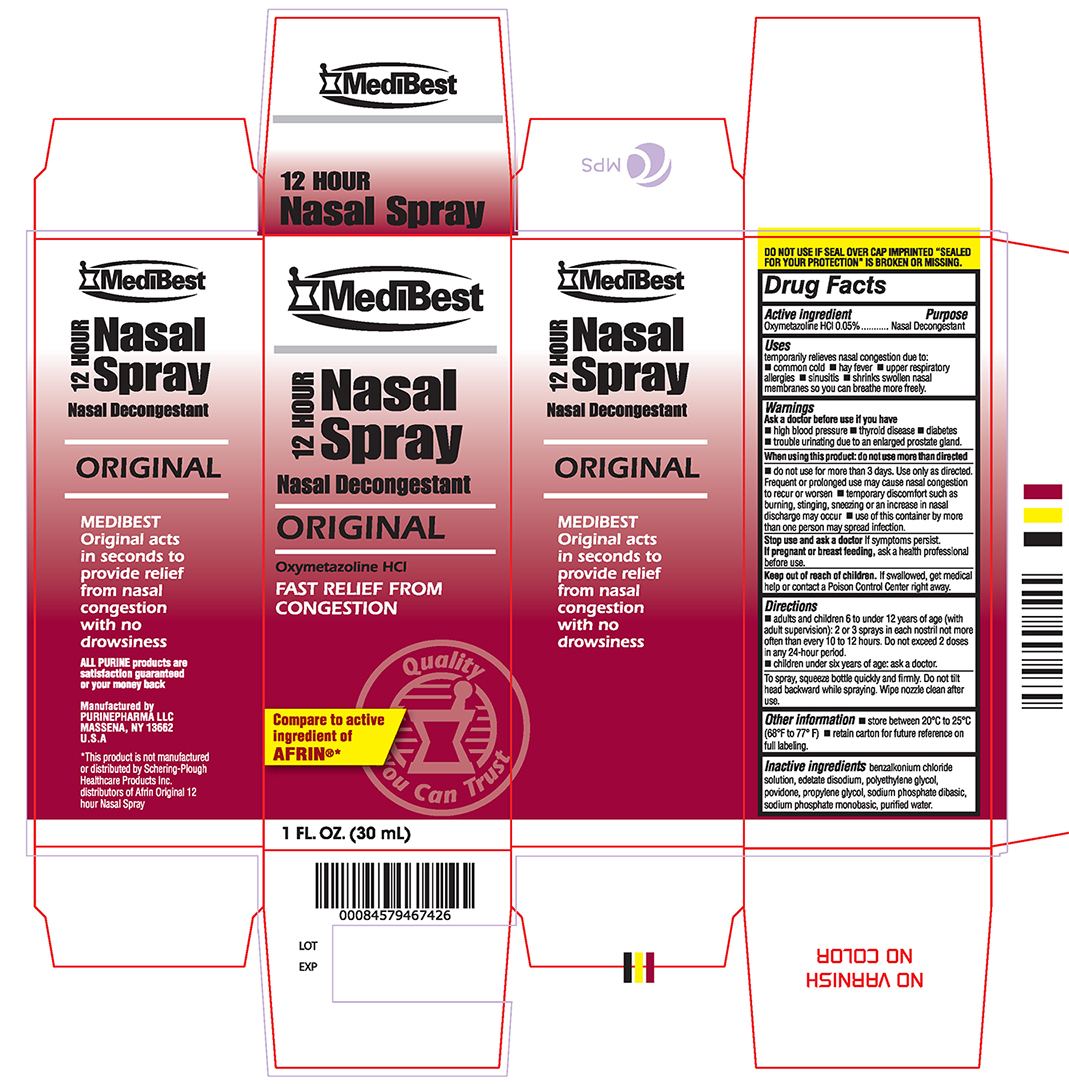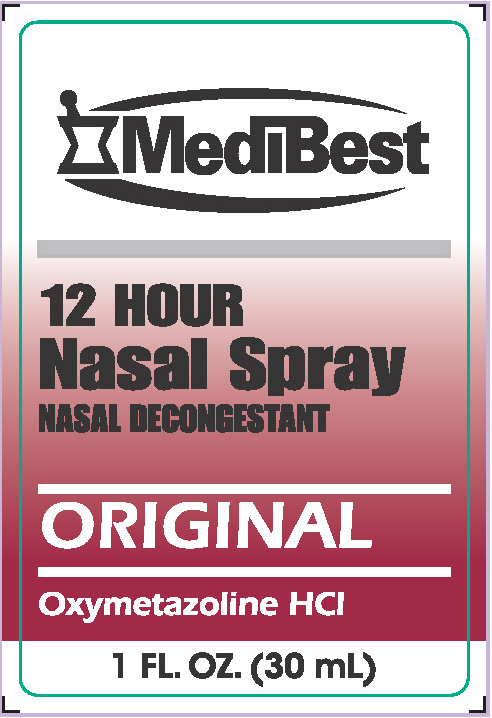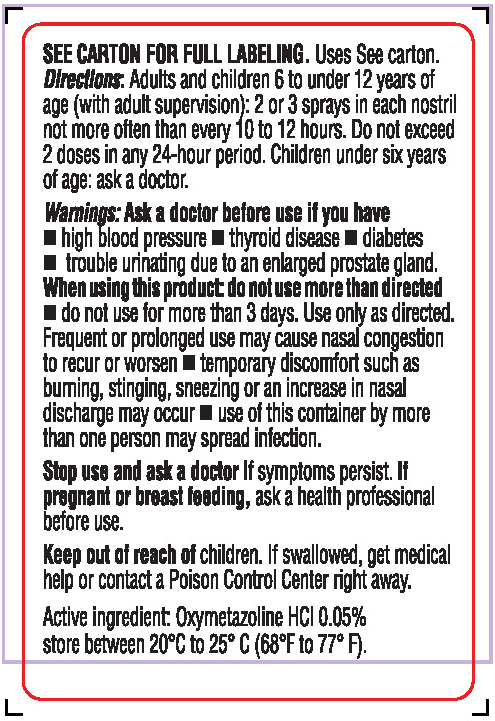 DRUG LABEL: OXYMETAZOLINE HCl
NDC: 58599-027 | Form: SPRAY
Manufacturer: PURINEPHARMA LLC
Category: otc | Type: HUMAN OTC DRUG LABEL
Date: 20150213

ACTIVE INGREDIENTS: OXYMETAZOLINE HYDROCHLORIDE 0.5 mg/1 mL
INACTIVE INGREDIENTS: WATER; EDETATE DISODIUM; SODIUM PHOSPHATE, DIBASIC; SODIUM PHOSPHATE, MONOBASIC; POVIDONE K90; BENZALKONIUM CHLORIDE; POLYETHYLENE GLYCOL 400; PROPYLENE GLYCOL

NASAL SPRAY - ORIGINAL 15mL and 30mL

Active Ingredient: Oxymetazoline HCl 0.05%

Purpose: Nasal Decongestant

Uses
Temporarily relieves nasal congestion due to:

- common cold
- hay fever
- upper respiratory allergies
- sinusitis
- shrinks swollen nasal membrances so you can breathe more freely.

WARNINGS

Ask a doctor before use if you have

- high blood pressure
- thyroid disease
- diabetes
- trouble urinating due to an enlarged prostate gland

When using this product: do not use more than directed

Do not use for more than 3 days. Use only as directed.

When using this product

- Frequent or prolonged use may cause nasal congestion to rcur or worsen
- temporary discomfort such as buming, stinging, sneezing or an increase in nasal discharge may occur
- use of this container by more than one person may spread infection

Stop use and ask a doctor If symptoms persist. If pregnant or breast feeding, ask a health professional before use.

Keep out of reach of children. If swallowed, get medical help or contact a Poison Control Center right away.

DOSAGE AND ADMINISTRATION

Directions: Adults and children 6 to under 12 years of age (with adult supervision): 2 or 3 sprays in each nostrill not more often than every 10 to 12 hours. Do not exceed 2 doses in any 24-hour period.
Children under six years of age: ask a doctor.

To spray, squeeze bottle quickly and firmly. Do not tilt head backward while spraying. Wipe nozzle clean after use.

STORAGE AND HANDLING

Store between 20°C to 25°C (68° to 77° F)

Retain carton for future reference on full labeling.

INACTIVE INGREDIENT

Purified Water, Edetate Disodium, Sodium Phosphate Dibasic, Sodium Phosphate Monobasic, Povidone, Benzalkonium Chloride Solution, Polyethylene Glycol, Propylene Glycol

HOW SUPPLIED

NDC 58599-027-01: 30 mL in a Bottle, NDC 58599-027-17: 15 mL in a Bottle